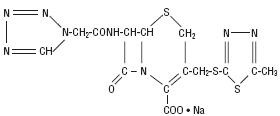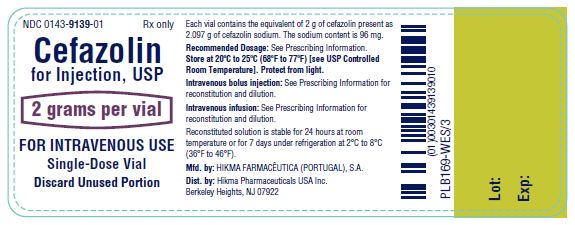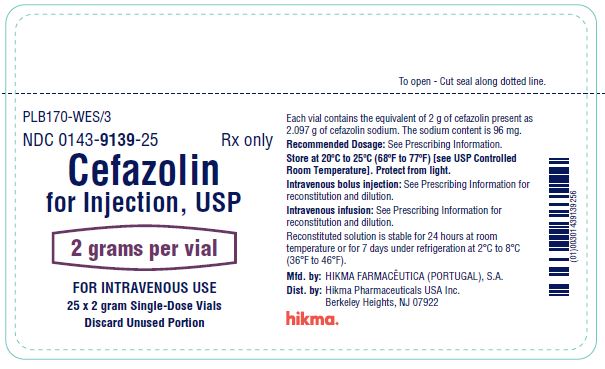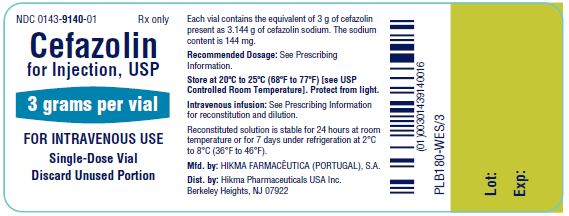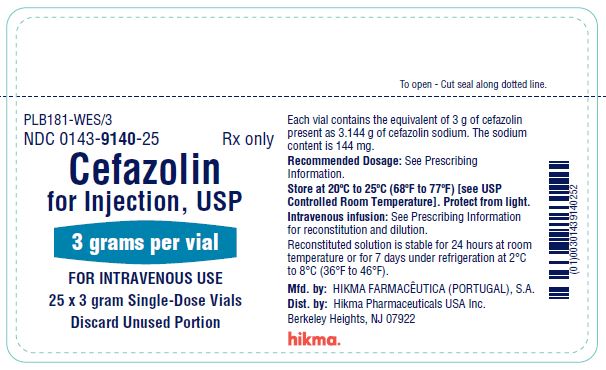 DRUG LABEL: Cefazolin
NDC: 0143-9139 | Form: INJECTION, POWDER, FOR SOLUTION
Manufacturer: Hikma Pharmaceuticals USA Inc.
Category: prescription | Type: HUMAN PRESCRIPTION DRUG LABEL
Date: 20241231

ACTIVE INGREDIENTS: CEFAZOLIN SODIUM 2 g/1 1

HIGHLIGHTS OF PRESCRIBING INFORMATION

These highlights do not include all the information needed to use CEFAZOLIN FOR INJECTION safely and effectively. See full prescribing information for CEFAZOLIN FOR INJECTION.
CEFAZOLIN for injection, for intravenous use
Initial U.S. Approval: 1973

RECENT MAJOR CHANGES

Dosage and Administration (2.1, 2.2, 2.3, 2.6) 12/2024

1 INDICATIONS AND USAGE

Cefazolin for Injection is a cephalosporin antibacterial indicated for:

- Treatment of the following infections caused by susceptible isolates of the designated microorganisms in adult and pediatric patients 1 month of age and older for whom appropriate dosing with this formulation can be achieved:
  - Respiratory tract infections (1.1)
  - Urinary tract infections (1.2)
  - Skin and skin structure infections (1.3)
  - Biliary tract infections (1.4)
  - Bone and joint infections (1.5)
  - Genital infections (1.6)
  - Septicemia (1.7)
  - Endocarditis (1.8)
- Perioperative prophylaxis in adult patients (1.9)

To reduce the development of drug-resistant bacteria and maintain the effectiveness of Cefazolin for Injection and other antibacterial drugs, Cefazolin for Injection should be used only to treat or prevent infections that are proven or strongly suspected to be caused by bacteria (1.10)

2 DOSAGE AND ADMINISTRATION

Cefazolin for Injection, 2 grams/vial:

- For intravenous infusion (2.1)
- For intravenous bolus injection (2.1)
- Not for intramuscular administration (2.1)

Cefazolin for Injection, 3 grams/vial:

- For intravenous infusion only (2.1)
- Not for intravenous bolus injection administration or intramuscular administration (2.1)

Recommended Dosage in Adult Patients with CLcr that is greater than or equal to 55 mL/min (2.2)

Type of Infection | Dose | Frequency
Moderate to severe infections | 500 mg to 1 gram | every 6 to 8 hours
Mild infections caused by susceptible gram-positive cocci | 250 mg to 500 mg | every 8 hours
Acute, uncomplicated urinary tract infections | 1 gram | every 12 hours
Pneumococcal pneumonia | 500 mg | every 12 hours
Severe, life-threatening infections (e.g., endocarditis, septicemia)* | 1 gram to 1.5 grams | every 6 hours
Perioperative prophylaxis | 1 gram to 2 grams | 1/2 to 1 hour prior to start of surgery
Perioperative prophylaxis | 500 mg to 1 gram | during surgery for lengthy procedures (e.g., 2 hours or more)
Perioperative prophylaxis | 500 mg to 1 gram | every 6 to 8 hours for 24 hours postoperatively

* In rare instances, doses of up to 12 grams of cefazolin per day have been used.

Recommended Dosage in Pediatric Patients with CLcr that is greater than or equal to 70 mL/min (2.3)

Type of Infection | Dose | Frequency
Mild to moderately severe infections | 25 mg per kg to 50 mg per kg | divided into 3 or 4 equal doses
Severe infections | May increase to 100 mg per kg | divided into 3 or 4 equal doses

- Dosage adjustment is required for adult patients with CLcr that is less than 55 mL/min and pediatric patients with CLcr that is less than 70 mL/min (2.4)
- See full prescribing information for preparation and administration instructions (2.6)

3 DOSAGE FORMS AND STRENGTHS

For Injection: 2 grams or 3 grams of cefazolin as a powder in single-dose vial for reconstitution (3)

4 CONTRAINDICATIONS

Hypersensitivity to cefazolin or other cephalosporin class antibacterial drugs, penicillins, or other beta-lactams (4)

5 WARNINGS AND PRECAUTIONS

- Hypersensitivity Reactions: Cross-hypersensitivity may occur in up to 10% of patients with a history of penicillin allergy. If an allergic reaction occurs, discontinue the drug (5.1)
- Clostridioides difficile-Associated Diarrhea (CDAD): May range in severity from mild to fatal colitis. Evaluate if diarrhea occurs. (5.3)
- Prothrombin Activity: May be associated with a fall in prothrombin activity. Prothrombin time should be monitored in patients at risk and exogenous vitamin K administered as indicated (5.5)

6 ADVERSE REACTIONS

Adult and Pediatric Patients: Most common adverse reactions are gastrointestinal (nausea, vomiting, diarrhea), and allergic reactions (anaphylaxis, skin rash) (6)

To report SUSPECTED ADVERSE REACTIONS, contact Hikma Pharmaceuticals USA Inc. at 1-877-845-0689, or the FDA at 1-800-FDA-1088 or www.fda.gov/medwatch.

7 DRUG INTERACTIONS

Probenecid: The renal excretion of cefazolin is inhibited by probenecid. Co-administration of probenecid with Cefazolin for Injection is not recommended (7)

12.4 Microbiology

To reduce the development of drug-resistant bacteria and maintain the effectiveness of cefazolin for injection and other antibacterial drugs, cefazolin for injection should be used only to treat or prevent infections that are proven or strongly suspected to be caused by bacteria. (1.10).

FULL PRESCRIBING INFORMATION

RECENT MAJOR CHANGES

Dosage and Administration (2.1, 2.2, 2.3, 2.6) 06/2024

1 INDICATIONS AND USAGE

1.1 Respiratory Tract Infections

Cefazolin for Injection is indicated for the treatment of respiratory tract infections due to Streptococcus pneumoniae, Klebsiella species, Hemophilus influenzae, Staphylococcus aureus (methicillin-susceptible), and Group A beta-hemolytic streptococciin adults and pediatric patients 1 month of age and older for whom appropriate dosing with this formulation can be achieved [see Dosage and Administration (2.1, 2.2, 2.4 and 2.5)].

Limitations of Use

Injectable benzathine penicillin is considered to be the drug of choice in treatment and prevention of streptococcal infections, including the prophylaxis of rheumatic fever.

Cefazolin for Injection is indicated for the eradication of streptococci from the nasopharynx; however, data establishing the efficacy of Cefazolin for Injection in the subsequent prevention of rheumatic fever are not available at present.

1.2 Urinary Tract Infections

Cefazolin for Injection is indicated for the treatment of urinary tract infections due to Escherichia coli, Proteus mirabilis, and Klebsiella species (spp.) in adults and pediatric patients 1 month of age and older for whom appropriate dosing with this formulation can be achieved [see Dosage and Administration (2.1, 2.2, 2.4 and 2.5)].

1.3 Skin and Skin Structure Infections

Cefazolin for Injection is indicated for the treatment of skin and skin structure infections due to S. aureus (methicillin-susceptible), Group A beta-hemolytic streptococci, and Streptococcus species (spp.) in adults and pediatric patients 1 month of age and older for whom appropriate dosing with this formulation can be achieved [see Dosage and Administration (2.1, 2.2, 2.4 and 2.5)].

1.4 Biliary Tract Infections

Cefazolin for Injection is indicated for the treatment of biliary tract infections due to E. coli, various isolates of Streptococcus spp., P. mirabilis, Klebsiella spp., and S. aureus (methicillin-susceptible) in adults and pediatric patients 1 month of age and older for whom appropriate dosing with this formulation can be achieved [see Dosage and Administration (2.1, 2.2, 2.4 and 2.5)].

1.5 Bone and Joint Infections

Cefazolin for Injection is indicated for the treatment of bone and joint infections due to S. aureus in adults and pediatric patients 1 month of age and older for whom appropriate dosing with this formulation can be achieved [see Dosage and Administration (2.1, 2.2, 2.4 and 2.5)].

1.6 Genital Infections

Cefazolin for Injection is indicated for the treatment of genital infections (i.e., prostatitis, epididymitis) due to E. coli, P. mirabilis, and Klebsiella species in adults and pediatric patients 1 month of age and older for whom appropriate dosing with this formulation can be achieved [see Dosage and Administration (2.1, 2.2, 2.4 and 2.5)].

1.7 Septicemia

Cefazolin for Injection is indicated for the treatment of septicemia due to S. pneumoniae, S. aureus (methicillin-susceptible), P. mirabilis, E. coli, and Klebsiella species in adults and pediatric patients 1 month of age and older for whom appropriate dosing with this formulation can be achieved [see Dosage and Administration (2.1, 2.2, 2.4 and 2.5)].

1.8 Endocarditis

Cefazolin for Injection is indicated for the treatment of endocarditis due to S. aureus (methicillin-susceptible) and Group A beta-hemolytic streptococci in adults and pediatric patients 1 month of age and older for whom appropriate dosing with this formulation can be achieved [see Dosage and Administration (2.1, 2.2, 2.4 and 2.5)].

1.9 Perioperative Prophylaxis

Cefazolin for Injection is indicated for perioperative prophylaxis in adults. The prophylactic administration of Cefazolin for Injection preoperatively, intraoperatively and postoperatively may reduce the incidence of certain postoperative infections in patients undergoing surgical procedures which are classified as contaminated or potentially contaminated (e.g., vaginal hysterectomy, and cholecystectomy in high-risk patients such as those older than 70 years, with acute cholecystitis, obstructive jaundice, or common duct bile stones).

The perioperative use of Cefazolin for Injection is indicated in surgical patients in whom infection at the operative site would present a serious risk (e.g., during open-heart surgery and prosthetic arthroplasty).

The prophylactic administration of Cefazolin for Injection should usually be discontinued within a 24-hour period after the surgical procedure. In surgery where the occurrence of infection may be particularly devastating (e.g., open-heart surgery and prosthetic arthroplasty), the prophylactic administration of Cefazolin for Injection may be continued for 3 to 5 days following the completion of surgery.

If there are signs of infection, specimens for cultures should be obtained for the identification of the causative organism so that appropriate therapy may be instituted [see Dosage and Administration (2.3)].

1.10 Usage

To reduce the development of drug-resistant bacteria and maintain the effectiveness of Cefazolin for Injection and other antibacterial drugs, Cefazolin for Injection should be used only to treat or prevent infections that are proven or strongly suspected to be caused by susceptible bacteria. When culture and susceptibility information are available, they should be considered in selecting or modifying antibacterial therapy. In the absence of such data, local epidemiology and susceptibility patterns may contribute to the empiric selection of therapy.

2 DOSAGE AND ADMINISTRATION

2.1 Important Administration Instructions

- Cefazolin for Injection, 2 grams/vial:

Cefazolin for Injection, 2 grams/vial, is for intravenous infusion or intravenous bolus injection in adult and pediatric patients [see Dosage and Administration (2.2, 2.3, and 2.6)]. Not for intramuscular administration.

- Cefazolin for Injection, 3 grams/vial:

Cefazolin for Injection, 3 grams/vial, is for intravenous infusion only in adult and pediatric patients [see Dosage and Administration (2.2, 2.3, 2.5, and 2.6)]. Cefazolin for Injection, 3 grams/vial is not for intravenous bolus injection or intramuscular administration [see Dosage and Administration (2.5, 2.6)].

2.2 Recommended Dosage for the Treatment of Infections

Recommended Dosage for the Treatment of Infections in Adults with Creatinine Clearance (CLcr) Equal to 55 mL/min or Greater

The recommended adult dosages of Cefazolin for Injection for the treatment of infections [see Indications and Usage (1.1 to 1.8)] are outlined in Table 1 below.

Administration instructions are as follows:

- Cefazolin for Injection, 2 grams/vial is for intravenous infusion or intravenous bolus injection in adult patients [see Dosage and Administration (2.6)].
- Cefazolin for Injection, 3 grams/vial is only for intravenous infusion in adult patients.
- Cefazolin for Injection, 3 grams/vial is not for intravenous bolus injection in adult patients [see Dosage and Administration (2.6)].
- Cefazolin for Injection 2 grams/vial and 3 grams/vial are not for intramuscular injection.

Table 1: Recommended Dosage in Adult Patients with CLcr Equal to 55 mL/min or Greater
Site and Type of Infection | Dose | Frequency
Moderate to severe infections | 500 mg to 1 gram | every 6 to 8 hours
Mild infections caused by susceptible gram–positive cocci | 250 mg to 500 mg | every 8 hours
Acute, uncomplicated urinary tract infections | 1 gram | every 12 hours
Pneumococcal pneumonia | 500 mg | every 12 hours
Severe, life-threatening infections (e.g., endocarditis, septicemia)* | 1 gram to 1.5 grams | every 6 hours

*ln rare instances, doses of up to 12 grams of Cefazolin for Injection per day have been used.

Recommended Dosage for the Treatment of Infections in Pediatric Patients 1 Month of Age and Older with CLcr Equal to 70 mL/min or Greater

The recommended pediatric dosages for the treatment of infections [see Indications and Usage (1.1 to 1.8)] are outlined in Table 2 below.

Administration instructions are as follows:

- Cefazolin for Injection, 2 grams/vial is for intravenous infusion or intravenous bolus injection in pediatric patients [see Dosage and Administration (2.5, 2.6)].
- Cefazolin for Injection, 3 grams/vial is only for intravenous infusion in pediatric patients.
- Cefazolin for Injection, 3 grams/vial is not for intravenous bolus injection in pediatric patients [see Dosage and Administration (2.6)].
- Cefazolin for Injection 2 grams/vial and 3 grams/vial are not for intramuscular injection.

Table 2: Recommended Dosage in Pediatric Patients 1 Month of Age and Older with CLcr 70 mL/min or Greater for Treatment of Infections [see Indications and Usage (1.1 to 1.8)]
Type of Severity | Recommended Total Daily Dosage
Mild to moderately severe infections | 25 mg/kg to 50 mg/kg, divided into 3 or 4 equal doses
Severe infections | May increase to 100 mg/kg, divided into 3 or 4 equal doses

2.3 Recommended Dosage for Perioperative Prophylactic Use in Adults

Recommended Dosage for Perioperative Prophylaxis in Adults with CLcr Equal to 55 mL/min or Greater

To prevent postoperative infection in contaminated or potentially contaminated surgery, recommended dosages are described in Table 3 below.

Administration instructions are as follows:

- Cefazolin for Injection, 2 grams/vial is for intravenous infusion or intravenous bolus injection in adult patients [see Dosage and Administration (2.4, 2.6)].
- Cefazolin for Injection, 3 grams/vial is only for intravenous infusion in adult patients.
- Cefazolin for Injection, 3 grams/vial is not for intravenous bolus injection in adult patients [see Dosage and Administration (2.4, 2.6)].
- Cefazolin for Injection 2 grams/vial and 3 grams/vial are not for intramuscular injection.

Table 3: Recommended Dosage for Perioperative Prophylaxis in Adults with CLcr of 55 mL/min or Greater
Dose administered 1/2 hour to 1 hour prior to the start of surgery | Additional dose during lengthy operative procedures (e.g., 2 hours or more) | Dose for 24 hours post-operatively
1 gram to 2 grams | 500 mg to 1 gram | 500 mg to 1 gram every 6 hours to 8 hours

It is important that (1) the preoperative dose be given just (1/2 hour to 1 hour) prior to the start of surgery so that adequate antibacterial levels are present in the serum and tissues at the time of initial surgical incision; and (2) Cefazolin for Injection be administered, if necessary, at appropriate intervals during surgery to provide sufficient levels of the antibacterial drug at the anticipated moments of greatest exposure to infective organisms.

The perioperative prophylactic administration of cefazolin should usually be discontinued within a 24-hour period after the surgical procedure. In surgery where the occurrence of infection may be particularly devastating (e.g., open-heart surgery and prosthetic arthroplasty), the prophylactic administration of Cefazolin for Injection may be continued for 3 to 5 days following the completion of surgery.

2.4 Recommended Dosage in Adult and Pediatric Patients with Renal Impairment

Recommended Dosage in Adult Patients with CLcr less than 55 mL/min

The recommended dosage of Cefazolin for Injection in adult patients with renal impairment (CLcr less than 55 mL/min) is outlined in Table 4 below.

Table 4: Recommended Dosage in Adult Patients with CLcr Less than 55 mL/min
Creatinine Clearance | Dose | Frequency
35 to 54 mL/min | Recommended dose | every 8 hours or longer
11 to 34 mL/min | Half of recommended dose | every 12 hours
10 mL/min or less | Half of recommended dose | every 18 to 24 hours

*All reduced dosage recommendations apply after an initial loading dose appropriate to the severity of the infection.

Recommended Dosage in Pediatric Patients 1 Month of Age and Older with CLcr less than 70 mL/min

The recommended dosage of Cefazolin for Injection in pediatric patients 1 month of age and older with renal impairment (CLcr less than 70 mL/min) is outlined in Table 5 below.

Table 5: Recommended Dosage in Pediatric Patients 1 Month of Age and Older with CLcr Less than 70 mL/min
Creatinine Clearance | Recommended Dosage
40 to 70 mL/min | 60% of the normal daily dose given in equally divided doses every 12 hours
20 to 40 mL/min | 25% of the normal daily dose given in equally divided doses every 12 hours
5 to 20 mL/min | 10% of the normal daily dose every 24 hours

*All dosage recommendations apply after an initial loading dose.

2.5 Pediatric Dosage Preparation Guide

Table 6: Pediatric Dosage Guide 25 mg/kg/day Divided into 3 Doses

Weight | 25 mg/kg/day Divided into 3 Doses
Kg | Approximate Single Dose mg/every 8 hours | Volume (mL) needed with dilution of 136 mg/mL | Dose (mL) from final concentration 40 mg/mL | Dose (mL) from final concentration 30 mg/mL | Dose (mL) from final concentration 20 mg/mL
4.5 | 40 mg | 0.29 mL | 1 | 1.3 | 2
9 | 75 mg | 0.55 mL | 1.9 | 2.5 | 3.8
13.6 | 115 mg | 0.85 mL | 2.9 | 3.8 | 5.8
18.1 | 150 mg | 1.1 mL | 3.8 | 5 | 7.5
22.7 | 190 mg | 1.4 mL | 4.8 | 6.3 | 9.5

Table 7: Pediatric Dosage Guide 25 mg/kg/day Divided into 4 Doses

Weight | 25 mg/kg/day Divided into 4 Doses
Kg | Approximate Single Dose mg/every 6 hours | Volume (mL) needed with dilution of 136 mg/mL | Dose (mL) from final concentration 40 mg/mL | Dose (mL) from final concentration 30 mg/mL | Dose (mL) from final concentration 20mg/mL
4.5 | 30 mg | 0.22 mL | 0.8 | 1 | 1.5
9 | 55 mg | 0.40 mL | 1.4 | 1.8 | 2.8
13.6 | 85 mg | 0.63 mL | 2.1 | 2.8 | 4.3
18.1 | 115 mg | 0.85 mL | 2.9 | 3.8 | 5.8
22.7 | 140 mg | 1.03 mL | 3.5 | 4.7 | 7

Table 8: Pediatric Dosage Guide 50 mg/kg/day Divided into 3 Doses

Weight | 50 mg/kg/day Divided into 3 Doses
Kg | Approximate Single Dose mg/every 8 hours | Volume (mL) needed with dilution of 136 mg/mL | Dose (mL) from final concentration 40 mg/mL | Dose (mL) from final concentration 30 mg/mL | Dose (mL) from final concentration 20 mg/mL
4.5 | 75 mg | 0.55 mL | 1.8 | 2.5 | 3.7
9 | 150 mg | 1.10 mL | 3.7 | 5 | 7.5
13.6 | 225 mg | 1.65 mL | 5.6 | 7.5 | 11.2
18.1 | 300 mg | 2.21 mL | 7.5 | 10 | 15
22.7 | 375 mg | 2.76 mL | 9.3 | 12.5 | 18.7

Table 9: Pediatric Dosage Guide 50 mg/kg/day Divided into 4 Doses

Weight | 50 mg/kg/day Divided into 4 Doses
Kg | Approximate Single Dose mg/every 6 hours | Volume (mL) needed with dilution of 136 mg/mL | Dose (mL) from final concentration 40 mg/mL | Dose (mL) from final concentration 30 mg/mL | Dose (mL) from final concentration 20 mg/mL
4.5 | 55 mg | 0.40 mL | 1.4 | 1.8 | 2.8
9 | 110 mg | 0.81 mL | 2.8 | 3.7 | 5.5
13.6 | 170 mg | 1.25 mL | 4.3 | 5.7 | 8.5
18.1 | 225 mg | 1.65 mL | 5.6 | 7.5 | 11.3
22.7 | 285 mg | 2.10 mL | 7.1 | 9.5 | 14.3

2.6 Preparation of Cefazolin for Injection

Parenteral drug products should be inspected visually for particulate matter and discoloration prior to administration, whenever solution and container permit. If particulate matter is evident in reconstituted fluids, the drug solutions should be discarded. Reconstituted solutions may range in color from pale yellow to yellow.

Reconstitution and Dilution

Intravenous Bolus Injection Administration (2g Vial only)

For preparation of intravenous bolus injection (2 grams/vial only) use the following steps:

- Reconstitute Cefazolin for Injection, 2 grams/vial single-dose vials with Sterile Water for Injection according to Table 10 below. Shake well until dissolved.
- Further dilute vials with an additional 11 mL Sterile Water for Injection and shake well.
- Inject the solution intravenously slowly, directly, or through tubing for patients receiving parenteral fluids as follows:
  - For 1 g dose, inject the solution intravenously slowly over 3 to 5 minutes and
  - For 2 g dose, inject the solution intravenously slowly over 7 to 11 minutes

Table 10: Volume and Concentration for Intravenous Bolus Injection Reconstitution (2 g vial only)
Cefazolin for Injection Vial Contents | Amount of Sterile Water for Injection for Reconstitution | Approximate Reconstituted Concentration | Approximate Available Volume
2 grams | 5.5 mL | 333 mg/mL | 6.6 mL

Pain associated with intravenous bolus administration has been reported with Cefazolin for Injection.

Intermittent or Continuous Intravenous Infusion

For intermittent or continuous intravenous infusion, reconstitute Cefazolin for Injection single-dose vials with Sterile Water for Injection according to Table 11 below and shake well. After reconstitution further dilute according to Table 11 using the following diluents:

For intermittent or continuous intravenous infusion: Dilute reconstituted Cefazolin for Injection in one of the following solutions:

- Sodium Chloride Injection, USP
- 5% Dextrose Injection, USP

Discard unused portion.

Table 11: Volumes for Reconstitution and Dilution and Final Concentrations for Intermittent or Continuous Intravenous Infusion
Cefazolin for Injection Vial Contents | Amount of Sterile Water for Injection for Reconstitution | Approximate Reconstituted Concentrations | Recommended Diluent Volume | Approximate Final Concentrations
2 grams | 15 mL | 136 mg/mL | 50 mL or; 100 mL | 40 mg/mL or; 20 mg/mL
3 grams | 15 mL | 196 mg/mL | 100 mL | 30 mg/mL

Storage of Reconstituted and Diluted Solutions

When reconstituted or diluted according to the instructions above, Cefazolin for Injection is stable for 24 hours at room temperature or for 7 days if stored under refrigeration at 2°C to 8°C (36°F to 46°F).

3 DOSAGE FORMS AND STRENGTHS

Cefazolin for Injection is available as 2 grams or 3 grams of cefazolin as a white to off-white crystalline powder in single-dose vial for reconstitution.

4 CONTRAINDICATIONS

Cefazolin for Injection is contraindicated in patients who have a history of immediate hypersensitivity reactions (e.g., anaphylaxis, serious skin reactions) to cefazolin or the cephalosporin class of antibacterial drugs, penicillins, or other beta-lactams [see Warnings and Precautions (5.1)].

5 WARNINGS AND PRECAUTIONS

5.1 Hypersensitivity Reactions to Cefazolin, Cephalosporins, Penicillins, or Other Beta-lactams

Serious and occasionally fatal hypersensitivity (anaphylactic) reactions have been reported in patients receiving beta-lactam antibacterial drugs. Before therapy with Cefazolin for Injection is instituted, careful inquiry should be made to determine whether the patient has had previous immediate hypersensitivity reactions to cefazolin, cephalosporins, penicillins, or carbapenems. Exercise caution if this product is to be given to penicillin-sensitive patients because cross-hypersensitivity among beta-lactam antibacterial drugs has been clearly documented and may occur in up to10% of patients with a history of penicillin allergy. If an allergic reaction to Cefazolin for Injection occurs, discontinue the drug.

5.2 Seizures in Patients with Renal Impairment

Seizures may occur with the administration of Cefazolin for Injection, particularly in patients with renal impairment when the dosage is not reduced appropriately. Discontinue Cefazolin for Injection if seizures occur or make appropriate dosage adjustments in patients with renal impairment [see Dosage and Administration (2.4)]. Anticonvulsant therapy should be continued in patients with known seizure disorders.

5.3 Clostridioides difficile-Associated Diarrhea

Clostridioides difficile-associated diarrhea (CDAD) has been reported with use of nearly all antibacterial agents, including cefazolin, and may range in severity from mild diarrhea to fatal colitis. Treatment with antibacterial agents alters the normal flora of the colon leading to overgrowth of C. difficile.

C. difficile produces toxins A and B, which contribute to the development of CDAD. Hypertoxin-producing isolates of C. difficile cause increased morbidity and mortality, as these infections can be refractory to antimicrobial therapy and may require colectomy. CDAD must be considered in all patients who present with diarrhea following antibacterial drug use. Careful medical history is necessary since CDAD has been reported to occur over two months after the administration of antibacterial agents.

If CDAD is suspected or confirmed, ongoing antibacterial drug use not directed against C. difficile may need to be discontinued. Appropriate fluid and electrolyte management, protein supplementation, antibacterial drug treatment of C. difficile, and surgical evaluation should be instituted as clinically indicated.

5.4 Risk of Development of Drug-resistant Bacteria

Prescribing Cefazolin for Injection in the absence of a proven or strongly suspected bacterial infection or a prophylactic indication is unlikely to provide benefit to the patient and increases the risk of the development of drug-resistant bacteria.

Prolonged use of Cefazolin for Injection may result in the overgrowth of nonsusceptible organisms. Careful clinical observation of the patient is essential.

5.5 Prothrombin Activity

Cephalosporins may be associated with a fall in prothrombin activity. Those at risk include patients with renal or hepatic impairment or poor nutritional state, as well as patients receiving a protracted course of antimicrobial therapy, and patients previously stabilized on anticoagulant therapy. Prothrombin time should be monitored in patients at risk and exogenous vitamin K administered as indicated.

5.6 Drug/Laboratory Test Interactions

Urinary glucose

A false positive reaction for glucose in the urine may occur with Benedict’s solution, Fehling’s solution or with CLINITEST® tablets, but not with enzyme-based tests such as CLINISTIX®.

Coombs Test

Positive direct and indirect antiglobulin (Coombs) tests have occurred; these may also occur in neonates whose mothers received cephalosporins before delivery.

6 ADVERSE REACTIONS

The following clinically significant adverse reactions to cefazolin for injection are described below and elsewhere in the labeling:

- Hypersensitivity reactions to Cefazolin, Cephalosporins, Penicillins, or Other Beta-lactams [see Warnings and Precautions (5.1)]
- Seizures in Patients with Renal Impairment [see Warnings and Precautions (5.2)]
- Clostridioides difficile-associated Diarrhea [see Warnings and Precautions (5.3)]
- Prothrombin Activity [see Warnings and Precautions (5.5)]

6.1 Clinical Trials Experience

Because clinical trials are conducted under widely varying conditions, adverse reaction rates observed in the clinical trials of a drug cannot be directly compared to rates in the clinical trials of another drug and may not reflect the rates observed in practice. The following reactions have been reported:

Gastrointestinal: Diarrhea, oral candidiasis (oral thrush), vomiting, nausea, stomach cramps, anorexia and Clostridioides difficile colitis. Onset of Clostridioides difficile colitis symptoms may occur during or after antibacterial treatment [see Warnings and Precautions (5.3)].

Allergic: Anaphylaxis, eosinophilia, itching, drug fever, skin rash, Stevens-Johnson syndrome.

Hematologic: Neutropenia, leukopenia, thrombocytopenia, thrombocythemia.

Hepatic: Transient rise in serum glutamic oxaloacetic transaminase (SGOT), serum glutamic pyruvic transaminase (SGPT), and alkaline phosphatase levels has been observed. Reports of hepatitis have been received.

Renal: Reports of increased BUN and creatinine levels, as well as renal failure, have been received.

Local Reactions: Instances of phlebitis have been reported at site of injection. Some induration has occurred.

Other Reactions: Pruritus (including genital, vulvar and anal pruritus, genital moniliasis, and vaginitis).

6.2 Postmarketing Experience

The following adverse reactions have been identified during post approval use of cefazolin. Because these reactions are reported voluntarily from a population of uncertain size, it is not always possible to reliably estimate their frequency or establish a causal relationship to drug exposure.

Immune system disorders: Serum sickness-like reaction

Renal and urinary disorders: Acute tubulointerstitial nephritis (ATIN)

Skin and subcutaneous tissue disorders: Acute generalized exanthematous pustulosis (AGEP)

6.3 Cephalosporin-class Adverse Reactions

In addition to the adverse reactions listed above that have been observed in patients treated with cefazolin, the following adverse reactions and altered laboratory tests have been reported for cephalosporin-class antibacterials:

Erythema multiforme, toxic epidermal necrolysis, renal impairment, toxic nephropathy, aplastic anemia, hemolytic anemia, hemorrhage, hepatic impairment including cholestasis, and pancytopenia.

7 DRUG INTERACTIONS

The renal excretion of cefazolin is inhibited by probenecid. Co-administration of probenecid with Cefazolin for Injection is not recommended.

8 USE IN SPECIFIC POPULATIONS

8.1 Pregnancy

Risk Summary

Available data from published prospective cohort studies, case series and case reports over several decades with cefazolin use in pregnant women have not established a drug-associated risk of major birth defects, miscarriage, or adverse maternal or fetal outcomes. These studies have methodologic limitations, including small sample size, retrospective study design, and inconsistent comparator groups. Cefazolin crosses the placenta.

Animal reproduction studies performed in rats, mice and rabbits administered cefazolin during organogenesis at doses 1 to 3 times the maximum recommended human dose (MRHD) did not demonstrate adverse developmental outcomes. In rats subcutaneously administered cefazolin prior to delivery and throughout lactation, there were no adverse effects on offspring at a dose approximately 2 times the MRHD (see Data)

The estimated background risk of major birth defects and miscarriage for the indicated population is unknown. All pregnancies have a background risk of birth defect, loss, or other adverse outcomes. In the U.S. general population, the estimated background risk of major birth defects and miscarriage in clinically recognized pregnancies is 2% to 4% and 15% to 20%, respectively.

Data

Animal Data

Reproduction studies have been performed in rats, mice and rabbits administered cefazolin subcutaneously during organogenesis at doses of 2000, 2400 and 240 mg/kg/day (approximately 1 to 3 times the maximum recommended human dose on a body surface area comparison). There was no evidence of any adverse effects on embryofetal development due to cefazolin. In a peri-postnatal study in rats, cefazolin administered subcutaneously up to 1200 mg/kg/day (approximately 2 times the MRHD based on body surface area comparison) to pregnant dams prior to delivery and through lactation caused no adverse effects on offspring.

8.2 Lactation

Risk Summary

Data from published literature report that cefazolin is present in human milk but is not expected to accumulate in a breastfed infant. There are no data on the effects of cefazolin on the breastfed child or on milk production. The developmental and health benefits of breastfeeding should be considered along with the mother’s clinical need for Cefazolin for Injection and any potential adverse effects on the breastfed child from Cefazolin for Injection or from the underlying maternal condition.

8.4 Pediatric Use

Cefazolin for Injection is indicated for the treatment of respiratory tract infections, urinary tract infections, skin and skin structure infections, biliary tract infections, bone and joint infections, genital infections, septicemia, and endocarditis in pediatric patients 1 month of age and older for whom appropriate dosing with this formulation can be achieved [see Indications and Usage (1.1 to 1.8) and Dosage and Administration (2.2)].

Safety and effectiveness of Cefazolin for Injection in premature infants and neonates have not been established.

8.5 Geriatric Use

Of the 920 subjects who received cefazolin for injection in clinical studies, 313 (34%) were 65 years and over, while 138 (15%) were 75 years and over. No overall differences in safety or effectiveness were observed between these subjects and younger subjects. Other reported clinical experience has not identified differences in responses between the elderly and younger patients, but greater sensitivity of some older individuals cannot be ruled out.

This drug is known to be substantially excreted by the kidney, and the risk of toxic reactions to this drug may be greater in patients with impaired renal function. Because elderly patients are more likely to have decreased renal function, care should be taken in dose selection, and it may be useful to monitor renal function [see Dosage and Administration (2.4) and Warnings and Precautions (5.2)].

8.6 Renal Impairment

When Cefazolin for Injection is administered to patients with low urinary output because of impaired renal function, lower daily dosage is required [see Dosage and Administration (2.4)].

10 OVERDOSAGE

Accidental overdosage resulting in seizures may occur in patients with renal impairment who receive doses greater than the recommended dosage of Cefazolin for Injection [see Warnings and Precautions (5.2)]. If seizures associated with accidental overdosage occur, discontinue Cefazolin for Injection and give supportive treatment.

11 DESCRIPTION

Cefazolin for Injection contains cefazolin sodium, a semi-synthetic cephalosporin. It is the sodium salt of 3-{[(5-methyl-1,3,4-thiadiazol-2-yl)thio]-methyl}-8-oxo-7-[2-(1H-tetrazol-1-yl) acetamido]-5-thia-1-azabicyclo [4.2.0]oct-2-ene-2-carboxylic acid. The molecular formula is C14H13N8NaO4S3 and molecular weight is 476.49.

Structural Formula:

Structural Formula

Cefazolin for Injection is supplied as a sterile powder in single-dose vials.

The 2 g/vial Cefazolin for Injection contains 2 grams of cefazolin (equivalent to 2.097 g of cefazolin sodium). The 3 g/vial Cefazolin for Injection contains 3 grams of cefazolin (equivalent to 3.144 grams of cefazolin sodium).

The 2 g/vial Cefazolin for Injection contains 96 mg of sodium. The 3 g/vial Cefazolin for Injection contains 144 mg of sodium. After reconstitution with sterile water for injection, the drug product solution has a pH of 4.0 to 6.0.

Cefazolin for Injection, 2 grams/vial, is intended for intravenous infusion or intravenous bolus injection. Cefazolin for Injection, 2 grams/vial is not for intramuscular administration. Cefazolin for Injection, 3 grams/vial, is intended for intravenous infusion only. Cefazolin for Injection, 3 grams/vial is not for intravenous bolus injection or intramuscular administration in adult or pediatric patients [see Dosage and Administration (2.1, 2.2, 2.3)].

12 CLINICAL PHARMACOLOGY

12.1 Mechanism of Action

Cefazolin is an antibacterial drug [see Microbiology (12.4)].

12.2 Pharmacodynamics

The pharmacokinetic/pharmacodynamic relationship for cefazolin has not been evaluated in patients.

12.3 Pharmacokinetics

Studies have shown that following intravenous administration of cefazolin for injection to normal volunteers, mean serum concentrations peaked at approximately 185 mcg/mL and were approximately 4 mcg/mL at 8 hours for a 1-gram dose.

In a study (using normal volunteers) of constant intravenous infusion with dosages of 3.5 mg/kg for 1 hour (approximately 250 mg) and 1.5 mg/kg the next 2 hours (approximately 100 mg), cefazolin for injection produced a steady serum level at the third hour of approximately 28 mcg/mL.

Studies in patients hospitalized with infections indicate that cefazolin for injection produces mean peak serum levels approximately equivalent to those seen in normal volunteers.

Distribution

Bile levels in patients without obstructive biliary disease can reach or exceed serum levels by up to five times; however, in patients with obstructive biliary disease, bile levels of cefazolin for injection are considerably lower than serum levels (< 1 mcg/mL).

In synovial fluid, the level of cefazolin for injection becomes comparable to that reached in serum at about 4 hours after drug administration. Studies of cord blood show prompt transfer of cefazolin for injection across the placenta. Cefazolin for injection is present in very low concentrations in the milk of nursing mothers.

Elimination

The serum half-life for cefazolin for injection is approximately 1.8 hours following IV administration.

Excretion

Cefazolin for injection is excreted unchanged in the urine. In the first 6 hours approximately 60% of the drug is excreted in the urine and this increases to 70% to 80% within 24 hours.

Specific Populations

Patients with Renal Impairment

In patients undergoing peritoneal dialysis (2 L/hr.), cefazolin for injection produced mean serum levels of approximately 10 and 30 mcg/mL after 24 hours’ instillation of a dialyzing solution containing 50 mg/L and 150 mg/L, respectively. Mean peak levels were 29 mcg/mL (range 13 to 44 mcg/mL) with 50 mg/L (3 patients), and 72 mcg/mL (range 26 to 142 mcg/mL) with 150 mg/L (6 patients).

12.4 Microbiology

Mechanism of Action

Cefazolin is a bactericidal agent that acts by inhibition of bacterial cell wall synthesis.

Resistance

Predominant mechanisms of bacterial resistance to cephalosporins include the presence of extended-spectrum beta-lactamases and enzymatic hydrolysis. Methicillin-resistant staphylococci are uniformly resistant to cefazolin. Most isolates of indole positive Proteus (Proteus vulgaris), Enterobacter spp. (including Klebsiella aerogenes), Morganella morganii, Providencia rettgeri, Serratia spp., and Pseudomonas spp. are resistant to cefazolin.

Antimicrobial Activity

Cefazolin has been shown to be active against most isolates of the following microorganisms, both in vitro and in clinical infections [see Indications and Usage (1)]:

Aerobic bacteria

Gram-positive bacteria

Staphylococcus aureus (methicillin susceptible)

Staphylococcus epidermidis (methicillin susceptible)

Group A beta-hemolytic streptococci

Streptococcus pneumoniae

Streptococcus species

Gram-negative bacteria

Escherichia coli

Hemophilus influenzae

Klebsiella species

Proteus mirabilis

Susceptibility Test Methods

For specific information regarding susceptibility test interpretive criteria and associated test methods and quality control standards recognized by FDA for this drug, please see: https://www.fda.gov/STIC.

13 NONCLINICAL TOXICOLOGY

13.1 Carcinogenesis and Mutagenesis, Impairment of Fertility

Carcinogenicity and Mutagenesis

Mutagenicity studies and long-term studies in animals to determine the carcinogenic potential of Cefazolin for Injection have not been performed.

Impairment of Fertility

Fertility studies conducted in rats subcutaneously administered cefazolin at doses of 2000 mg/kg/day (approximately 3 times the maximum recommended human dose based on body surface area comparison) showed no impairment of mating and fertility.

16 HOW SUPPLIED

Cefazolin for Injection is available as 2 grams or 3 grams of cefazolin as a white to off-white crystalline powder in single-dose vial for reconstitution.

Cefazolin for Injection, USP | Packaged | NDC No.
2 grams/vial | Carton of 25 vials | 0143-9139-25
3 grams/vial | Carton of 25 vials | 0143-9140-25

Before reconstitution protect from light and store at 20°C to 25°C (68°F to 77°F) [see USP Controlled Room Temperature]. Storage conditions for reconstituted and diluted solutions of Cefazolin for Injection are described in another section of labeling [see Dosage and Administration (2.6)].

17 PATIENT COUNSELING INFORMATION

Serious Allergic Reactions

Advise patients that allergic reactions, including serious allergic reactions could occur and that serious reactions require immediate treatment and discontinuation of Cefazolin for Injection. Patients should report to their health care provider any previous allergic reactions to cefazolin, cephalosporins, penicillins, or other similar antibacterials [see Warnings and Precautions (5.1)].

Seizures

Advise patients that seizures could occur with Cefazolin for Injection. Instruct patients to inform a healthcare provider at once of any signs and symptoms of seizures, for immediate treatment, dosage adjustment, or discontinuation of Cefazolin for Injection [see Warnings and Precautions (5.2)].

Diarrhea

Advise patients that diarrhea is a common problem caused by antibacterials, which usually ends when the antibacterial is discontinued. Sometimes after starting treatment with antibacterials, patients can develop watery and bloody stools (with or without stomach cramps and fever) even as late as two or more months after having taken the last dose of the antibacterials. If this occurs, patients should contact a physician as soon as possible [see Warnings and Precautions (5.3)].

Antibacterial Resistance

Patients should be counseled that antibacterial drugs including Cefazolin for Injection, should only be used to treat bacterial infections. They do not treat viral infections (e.g., the common cold). When Cefazolin for Injection is prescribed to treat a bacterial infection, patients should be told that although it is common to feel better early in the course of therapy, the medication should be taken exactly as directed. Skipping doses or not completing the full course of therapy may: (1) decrease the effectiveness of the immediate treatment, and (2) increase the likelihood that bacteria will develop resistance and will not be treatable by Cefazolin for Injection or other antibacterial drugs in the future [see Warnings and Precautions (5.4)].

Manufactured by

HIKMA FARMACÊUTICA (PORTUGAL), S.A.

Estrada do Rio da Mó, 8, 8A e 8B – Fervença – 2705-906 Terrugem SNT, PORTUGAL

Distributed by

Hikma Pharmaceuticals USA Inc.

Berkeley Heights, NJ 07922

CLINITEST is a registered trademark of Miles, Inc.

CLINISTIX is a registered trademark of Bayer Corporation.

PIN609-WES/3

PRINCIPAL DISPLAY PANEL - 2 G

NDC 0143-9139-01 Rx only

Cefazolin

2 grams per vial

FOR INTRAVENOUS USE

Single-Dose Vial

Discard Unused Portion

NDC 0143-9139-25 Rx only

Cefazolin for Injection, USP

2 grams per vial

FOR INTRAVENOUS USE

25 x 2 gram Single-Dose Vials

Discard Unused Portion

PRINCIPAL DISPLAY PANEL - 3 G

NDC 0143-9140-01 Rx only

Cefazolin

3 grams per vial

FOR INTRAVENOUS USE

Single-Dose Vial

Discard Unused Portion

NDC 0143-9140-25 Rx only

Cefazolin for Injection, USP

3 grams per vial

FOR INTRAVENOUS USE

25 x 3 gram Single-Dose Vials

Discard Unused Portion